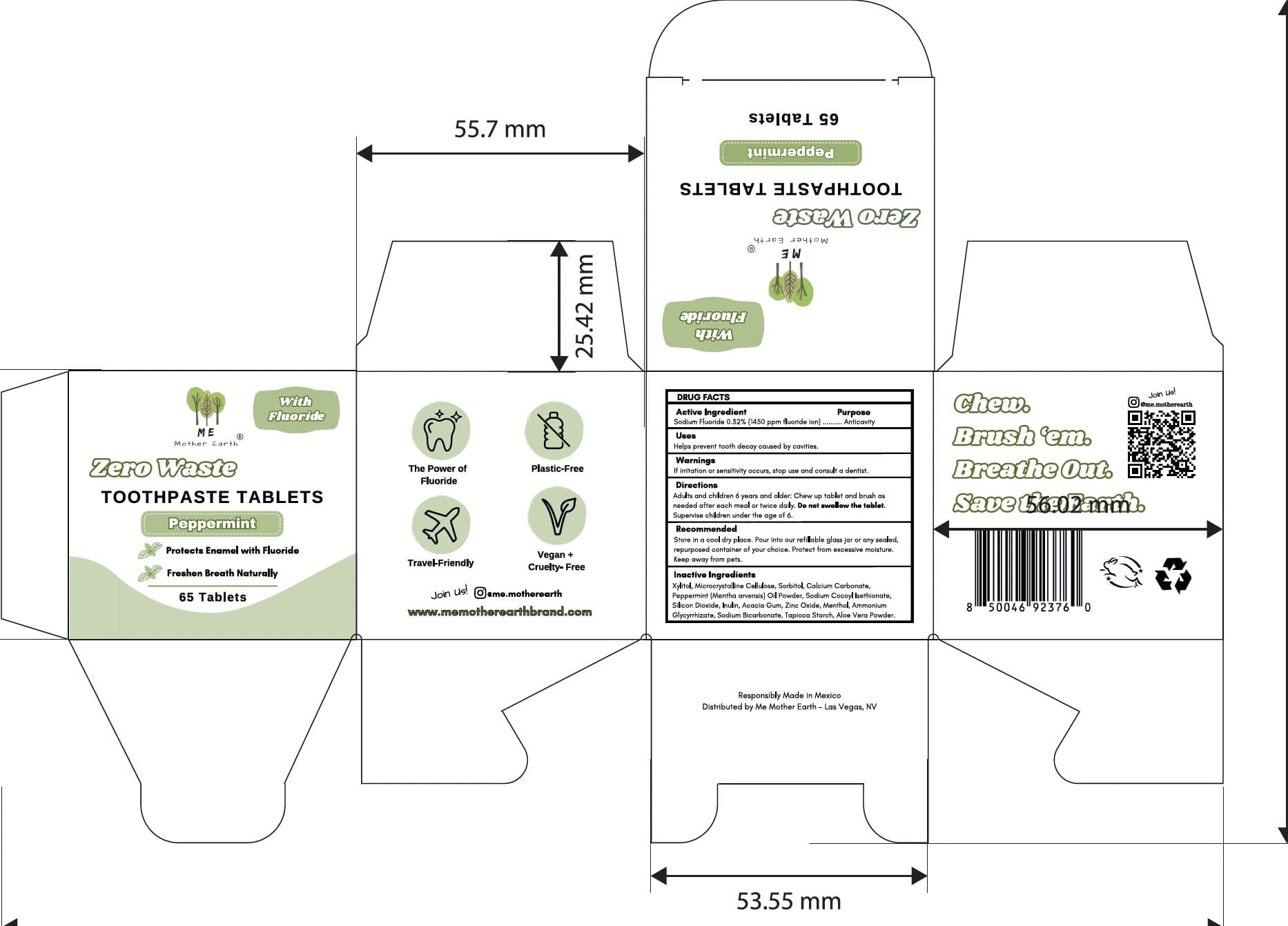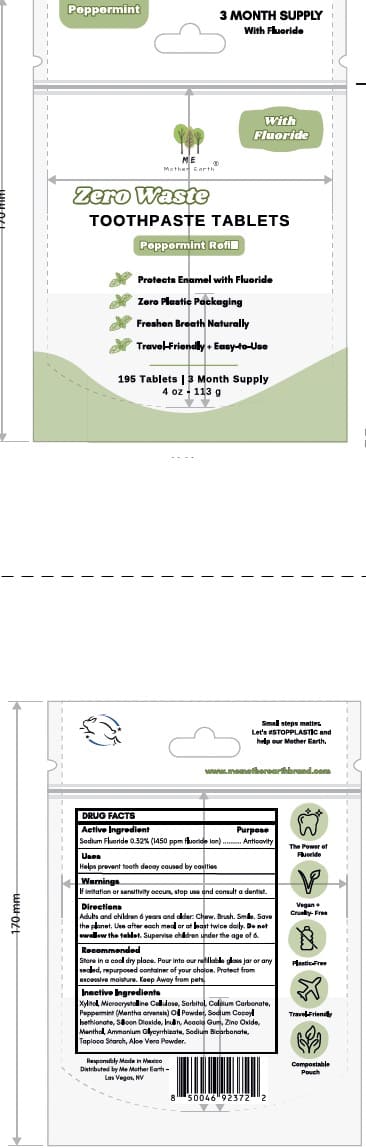 DRUG LABEL: ME MOTHER EARTH
NDC: 87232-444 | Form: TABLET, CHEWABLE
Manufacturer: A PLUS MERCHANDISE LLC
Category: otc | Type: HUMAN OTC DRUG LABEL
Date: 20251117

ACTIVE INGREDIENTS: SODIUM FLUORIDE 0.32 mg/1 1
INACTIVE INGREDIENTS: CALCIUM CARBONATE; ACACIA; AMMONIUM GLYCYRRHIZATE; SODIUM COCOYL ISETHIONATE; SILICON DIOXIDE; XYLITOL; ALOE VERA LEAF; CELLULOSE, MICROCRYSTALLINE; INULIN; MENTHOL; SODIUM BICARBONATE; STARCH, TAPIOCA; SORBITOL; PEPPERMINT OIL; ZINC CITRATE; CALCIUM HYDROXYAPATITE

MeMotherEarth-Muyme Peppermint Tabs 2025

Active Ingredient(s)

Sodium Fluoride 0.32% (1450 ppm fluoride ion) — Anticavity

Purpose

Anti-cavity

Use

Helps prevent tooth decay caused by cavities

Warnings

- If irritation or sensitivity occurs, stop use and consult a dentist.

KEEP OUT OF REACH OF CHILDREN

If more than used for brushing is accidentally swallowed, get medical help or contact a Poison Control Center immediately.

Directions

- Adults and children 6 years and older: Chew. Brush. Smile. Save the planet. Use after each meal or at least twice daily. Do not swallow the tablet. Supervise children under the age of 6.

Other information

Store in a cool dry place. Pour into our refillable glass jar or any sealed, repurposed container of your choice. Protect from excessive moisture. Keep away from pets.

Inactive ingredients

Xylitol, Microcrystalline Cellulose, Sorbitol, Calcium Carbonate, Peppermint (Mentha arvensis) Oil Powder, Sodium Cocoyl Isethionate, Silicon Dioxide, Inulin, Acacia Gum, Zinc Oxide, Menthol, Ammonium Glycyrrhizate, Sodium Bicarbonate, Tapioca Starch, Aloe Vera Powder.